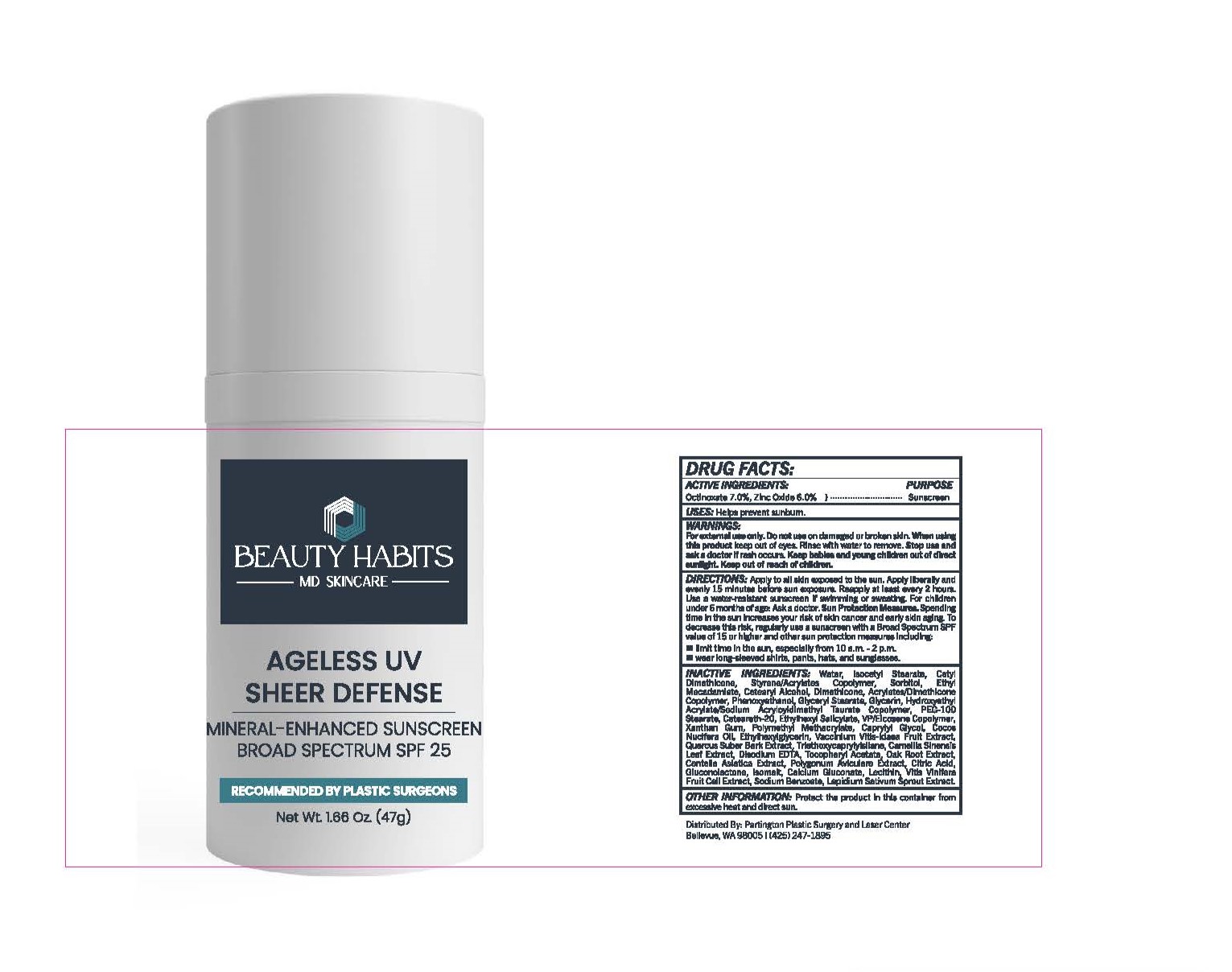 DRUG LABEL: Ageless UV Sheer Defense Mineral Enhanced Sunscreen Broad Spectrum SPF 25
NDC: 83877-2650 | Form: LOTION
Manufacturer: PARTINGTON PLASTIC SURGERY
Category: otc | Type: HUMAN OTC DRUG LABEL
Date: 20240228

ACTIVE INGREDIENTS: OCTINOXATE 7 g/100 mL; ZINC OXIDE 6 g/100 mL
INACTIVE INGREDIENTS: WATER; ISOCETYL STEARATE; SORBITOL; ETHYL MACADAMIATE; CETOSTEARYL ALCOHOL; DIMETHICONE; PHENOXYETHANOL; GLYCERYL MONOSTEARATE; GLYCERIN; HYDROXYETHYL ACRYLATE/SODIUM ACRYLOYLDIMETHYL TAURATE COPOLYMER (100000 MPA.S AT 1.5%); PEG-100 STEARATE; POLYOXYL 20 CETOSTEARYL ETHER; OCTISALATE; XANTHAN GUM; POLY(METHYL METHACRYLATE; 450000 MW); CAPRYLYL GLYCOL; ETHYLHEXYLGLYCERIN; LINGONBERRY; QUERCUS SUBER BARK; TRIETHOXYCAPRYLYLSILANE; GREEN TEA LEAF; EDETATE DISODIUM ANHYDROUS; .ALPHA.-TOCOPHEROL ACETATE; CENTELLA ASIATICA WHOLE; POLYGONUM AVICULARE TOP; CITRIC ACID MONOHYDRATE; GLUCONOLACTONE; ISOMALT; CALCIUM GLUCONATE; SODIUM BENZOATE; GARDEN CRESS SPROUT

Ageless UV Mineral Enhanced Sunscreen Broad Spectrum SPF 25

DRUG FACTS:

ACTIVE INGREDIENTS

Octinoxate 7.0%, Zinc Oxide 6.0%.

PURPOSE

Sunscreen

USES

Helps prevent sunburn.

WARNINGS

For external use only. Do not use on damaged or broken skin . When using this product keep out of eyes. Rinse with water to remove. Stop use and ask a doctor if rash occurs.

Keep out of reach of children.

DIRECTIONS

Apply to all skin exposed to the sun.

- Apply liberally and evenly 15 minutes before sun exposure.
- Reapply at least every 2 hours.
- Use a water-resistant sunscreen if swimming or sweating.
- For children under 6 months of age: Ask a doctor.

Sun Protection Measures. Spending time in the sun increases your risk of skin cancer and early skin aging. To decrease this risk, regularly use a sunscreen with a Broad Spectrum SPF value of 15 or higher and other sun protection measures including:

- limit time in the sun, especially from 10 a.m. - 2 p.m.
- wear long-sleeved shirts, pants, hats, and sunglasses.

INACTIVE INGREDIENTS

Water, Isocetyl Stearate, Cetyl Dimethicone, Styrene/Acrylates Copolymer, Sorbitol, Ethyl Macadamiate, Cetearyl Alcohol, Dimethicone, Acrylates/Dimethicone Copolymer, Phenoxyethanol, Glyceryl Stearate, Glycerin, Hydroxyethyl Acrylate/ Sodium Acryloyldimethyl Taurate Copolymer, PEG-100 Stearate, Ceteareth-20, Ethylhexyl Salicylate, VP/Eicosene Copolymer, Xanthan Gum, Polymethyl Methacrylate, Caprylyl Glycol, Cocos Nucifera Oil, Ethylhexylglycerin, Vaccinium Vitis-Idaea Fruit Extract, Quercus Suber Bark Extract, Triethoxycaprylylsilane, Camellia Sinensis Leaf Extract, Disodium EDTA, Tocopheryl Acetate, Oak Root Extract, Centella Asiatica Extract, Polygonum Aviculare Extract, Citric Acid, Gluconolactone, Isomalt, Calcium Gluconate, Lecithin, Vitis Vinifera Fruit Cell Extract, Sodium Benzoate, Lepidium Sativum Sprout Extract.

OTHER INFORMATION

Protect the product in this container from excessive heat and direct sun.

PRINCIPAL DISPLAY PANEL

Stay AgelessDaily Moisturizer Sunscreen

Broad Spectrum SPF 25